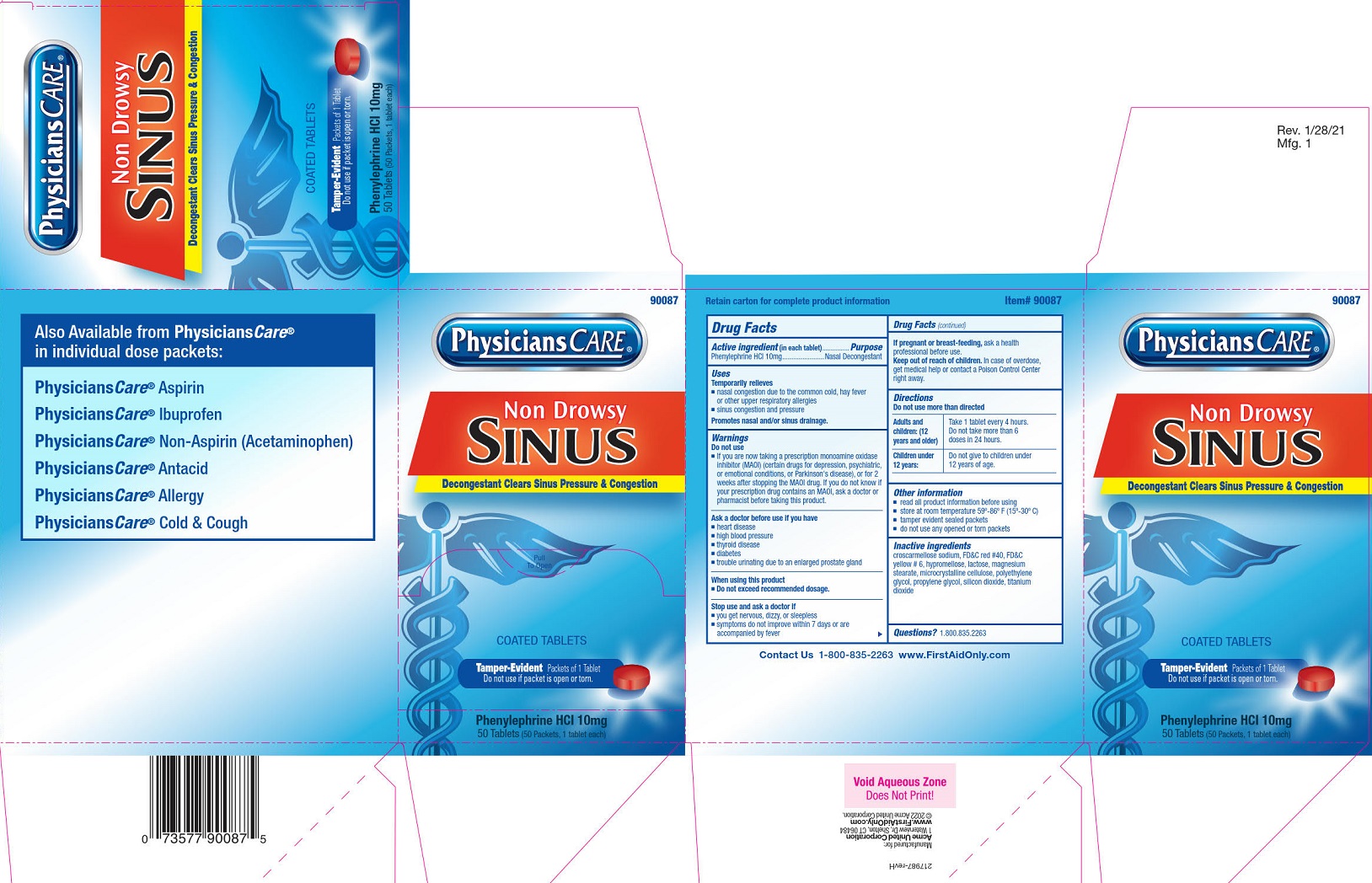 DRUG LABEL: PhysiciansCare Sinus
NDC: 0924-0133 | Form: TABLET, FILM COATED
Manufacturer: Acme United Corporation
Category: otc | Type: HUMAN OTC DRUG LABEL
Date: 20250908

ACTIVE INGREDIENTS: PHENYLEPHRINE HYDROCHLORIDE 10 mg/1 1
INACTIVE INGREDIENTS: CELLULOSE, MICROCRYSTALLINE; CROSCARMELLOSE SODIUM; FD&C RED NO. 40; FD&C YELLOW NO. 6; HYPROMELLOSES; LACTOSE; MAGNESIUM STEARATE; POLYETHYLENE GLYCOL 2000; PROPYLENE GLYCOL; SILICON DIOXIDE; TITANIUM DIOXIDE

PhysiciansCare Sinus

Drug Facts

Active ingredient (in each tablet)

Phenylephrine HCl 10mg

Purpose

Nasal Decongestant

Uses

Temporarily relieves

■ nasal congestion due to the common cold, hay fever or other upper respiratory allergies

■ sinus congestion and pressure

Promotes nasal and/or sinus drainage.

Warnings

Do not use

■ If you are now taking a prescription monoamine oxidase inhibitor (MAOI) (certain drugs for depression, psychiatric, or emotional conditions, or Parkinson's disease), or for 2 weeks after stopping the MAOI drug. If you do not know if your prescription drug contains an MAOI, ask a doctor or pharmacist before taking this product.

Ask a doctor before use if you have

■ heart disease

■ high blood pressure

■ thyroid disease

■ diabetes

■ trouble urinating due to an enlarged prostate gland

When using this product

■ do not exceed recommended dosage

Stop use and ask a doctor if

■ you get nervous, dizzy or sleepless

■ symptoms do not improve within 7 days or are accompanied by fever

PREGNANCY OR BREAST FEEDING

If pregnant or breast-feeding, ask a health professional before use.

KEEP OUT OF REACH OF CHILDREN

Keep out of the reach of children. In case of overdose, get medical help or contact a Poison Control Center right away.

Directions

■ do not use more than directed

Adults and children: (12 years and older) Take 1 tablet every 4 hours. Do not take more than 6 doses in 24 hours.

Children under 12 years: Do not give to children under 12 years of age

Other information

■ read all product information before using

■ store at room temperature 59º-86º F (15º-30º C)

■ tamper evident sealed packets

■ do not use any opened or torn packets

Inactive ingredients

croscarmellose sodium, FD&C red #40, FD&C yellow # 6, hypromellose, lactose, magnesium stearate, microcrystalline cellulose, polyethylene glycol, propylene glycol, silicon dioxide, titanium dioxide

Questions or comments?

1-800-835-2263

Physicians Care Sinus Label

980087

Physicians Care®

Non-Drowsy Sinus

Decongestant Clears Sinus Pressure & Congestion

Pull To Open

Coated Tablets

Tamper-Evident Packets of 1 Tablet

Do not use if packet is open or torn.

Phenylephrine HCl 10mg

50 Tabletsts (50 Packets, 1 tablet each)